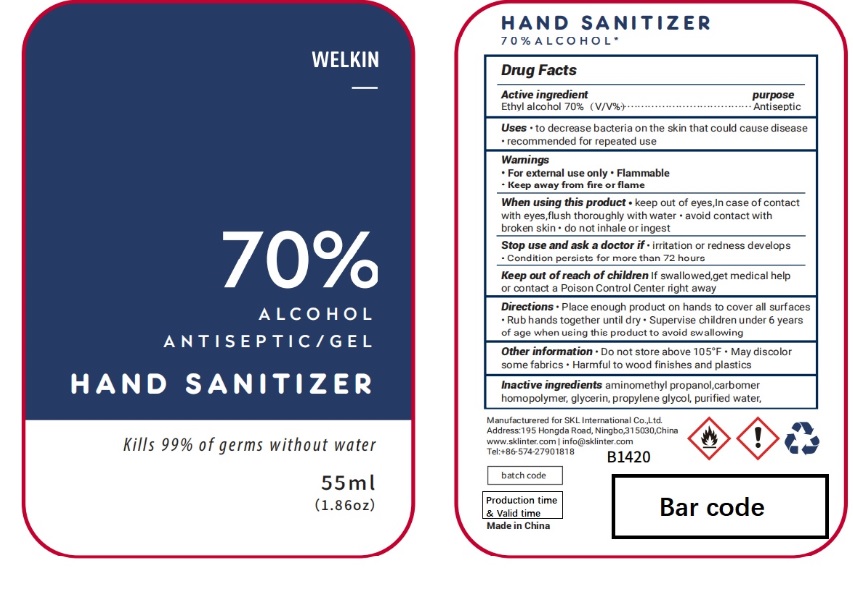 DRUG LABEL: WELKIN 70% Alcohol ANTISEPTIC
NDC: 74542-010 | Form: GEL
Manufacturer: Ningbo SKL International Co.,Ltd.
Category: otc | Type: HUMAN OTC DRUG LABEL
Date: 20200706

ACTIVE INGREDIENTS: ALCOHOL 70 mL/100 mL
INACTIVE INGREDIENTS: WATER; AMINOMETHYLPROPANOL; CARBOMER HOMOPOLYMER TYPE A; PROPYLENE GLYCOL; GLYCERIN

HAND SANITIZER

Active Ingredient

Ethyl Alcohol 70% v/v.

Purpose

Antiseptic

Uses

To decrease bacteria on the skin that could cause disease

Recommended for repeated use

Warnings

- For external use only
- Flammable
- Keep away from fire or flame

When using this product:

- Keep out of eyes. In case of contact with eyes, flush thoroughly with water.
- Avoid contact with broken skin.
- Do not inhale or ingest

Stop use and ask a doctor if:

- Irritation or redness develops
- Condition persists for more than 72 hours.

Keep out of reach of children

If swallowed, get medical help or contact a Poison Control Center right away.

Directions

- Place enough product on hand to cover all surfaces. Rub hands together until dry.
- Supervise children under 6 years of age when using this product to avoid swallowing.

Other information

- Do not store above 105℉
- May discolor some fabrics
- Harmful to wood finishes and plastics

Inactive ingredients

CARBOMER HOMOPOLYMER,PROPYLENE GLYCOL,AMINOMETHYLPROPANOL,GLYCERIN,WATER